DRUG LABEL: 70% Isopropyl Alcohol PE 1L
NDC: 79071-1001 | Form: LIQUID
Manufacturer: Riviera Beverages, LLC
Category: otc | Type: HUMAN OTC DRUG LABEL
Date: 20201018

ACTIVE INGREDIENTS: ISOPROPYL ALCOHOL 70 mL/100 mL
INACTIVE INGREDIENTS: WATER 30 mL/100 mL

70% Isopropyl Alcohol 1 Liter

Active Ingredients

Isopropyl Alcohol 70.00% v/v First Aid Antiseptic

Uses:

Helps prevent the risk of infection due to minor cuts, scraps and burns.

Warnings:

For External Use Only

Flammable-

Keep away from fire, flames, heat, sparks,electrical

Ask a Doctor before-

Use for deep or puncture wounds, Animal Bites or serious burns

When using this product-

Do not get into eyes, do not inhale, do not apply over large areas of the body, do not use longer than 1 week

Stop and ask a Doctor-

conditions persist or get worse

Keep out of reach of children-

If swallowed, get medical help or contact a Poison Control Center right away

Caution-

Fumes can be acutely irratating to skin, eyes and respitory system. Do not apply to irritated skin or if excessive irritation develops. Avoid getting into eyes or on mucous membranes. Avoid inhaling this product.

Directions-

Clean affected area- apply a small amount of this product on the area 1 to 3 times a day, may be covered with a sterile bandage, if bandaged, let dry first.

Other Information:

Does not contain nor is intented as a substitute for grain or ethyl alcohol.

Inactive Ingredients:

Water (USP)

Uses

To prevent risk of infection